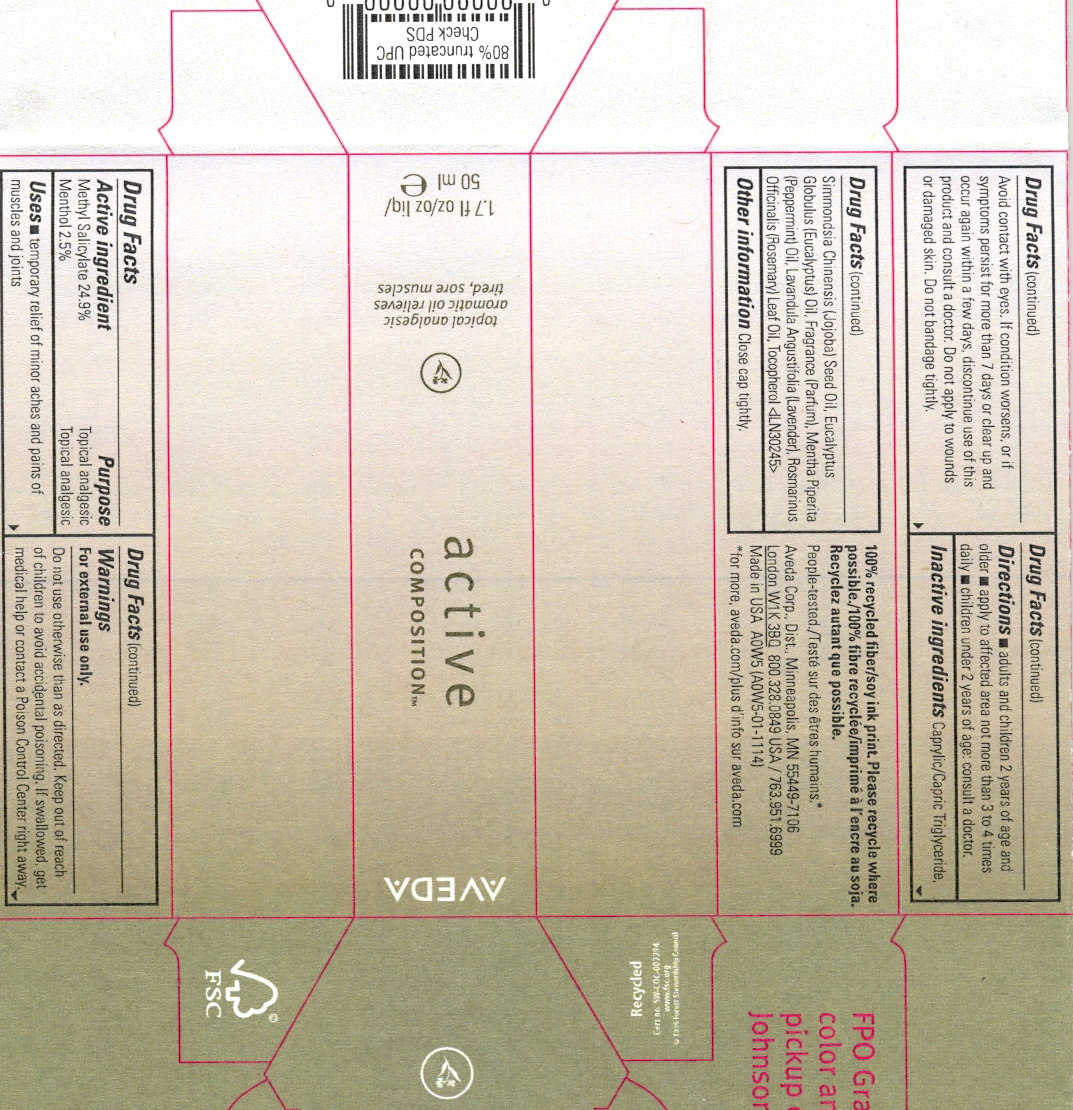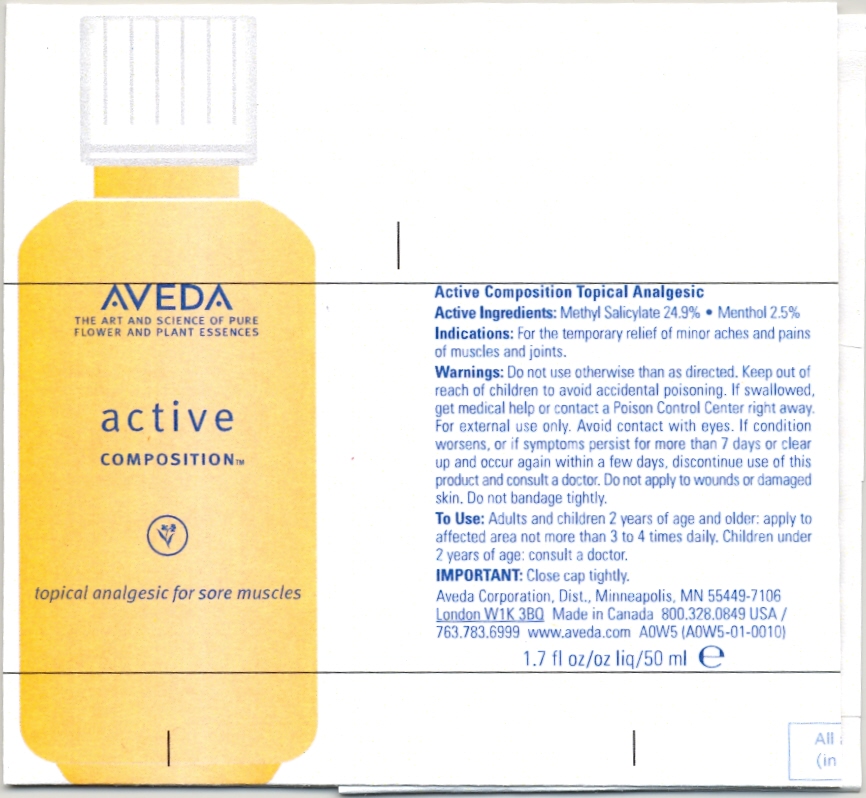 DRUG LABEL: Aveda Active Composition
NDC: 57677-005 | Form: LIQUID
Manufacturer: Aveda Corporation
Category: otc | Type: HUMAN OTC DRUG LABEL
Date: 20110308

ACTIVE INGREDIENTS: MENTHOL 1.25 mL/50 mL; METHYL SALICYLATE 12.45 mL/50 mL
INACTIVE INGREDIENTS: MEDIUM-CHAIN TRIGLYCERIDES 28.5 mL/50 mL; JOJOBA OIL 2.5 mL/50 mL; CAJUPUT OIL 0.75 mL/50 mL; EUCALYPTUS OIL 0.75 mL/50 mL; LAVENDER OIL 0.75 mL/50 mL; CITRUS AURANTIUM LEAFY TWIG OIL 0.75 mL/50 mL; PEPPERMINT OIL 0.625 mL/50 mL; CAMPHOR OIL 0.5 mL/50 mL; GERANIUM OIL, ALGERIAN TYPE 0.375 mL/50 mL; SWEET MARJORAM OIL 0.375 mL/50 mL; ROSEMARY OIL 0.375 mL/50 mL; ALPHA-TOCOPHEROL 0.05 mL/50 mL

AVEDA ACTIVE COMPOSITION

ACTIVE INGREDIENT

Methyl Salicylate 24.9% - Menthol 2.5% (Topical Analgesics)

PURPOSE

Indications: For the temporary relief of minor aches and pains of muscles and joints.

WARNINGS

Warnings: For external use only. Do not use otherwise than as directed.

Keep out of reach of children to avoid accidental poisoning.

ASK DOCTOR

If swallowed, get medical help or contact a Poison Control Center right away.

GENERAL PRECAUTIONS

For external use only. Avoid contact with eyes.

STOP USE

If condition worsens, or if symptoms persist for more that 7 days or clear up and occur again within a few days, discontinue use of this product and consult a doctor.

DO NOT USE

Do not apply to wounds or damaged skin. Do not bandage tightly.

DOSAGE AND ADMINISTRATION

Directions: Adults and children 2 years of age and older, apply to affected area not more that 3 to 4 times daily. Children under 2 years of age: consult a doctor.

INDICATIONS AND USAGE

Topical Analgesic, Aromatic oil relieves tired, sore muscles.

INACTIVE INGREDIENT

Caprylic/capric triglyceride

HOW SUPPLIED

Aveda Corp. Dist. Minneapolis, MN 55449-7106. London W1K 3B0. Made in Canada.

QUESTIONS

800-328-0849 USA / 763-783-6999. www.Aveda.com